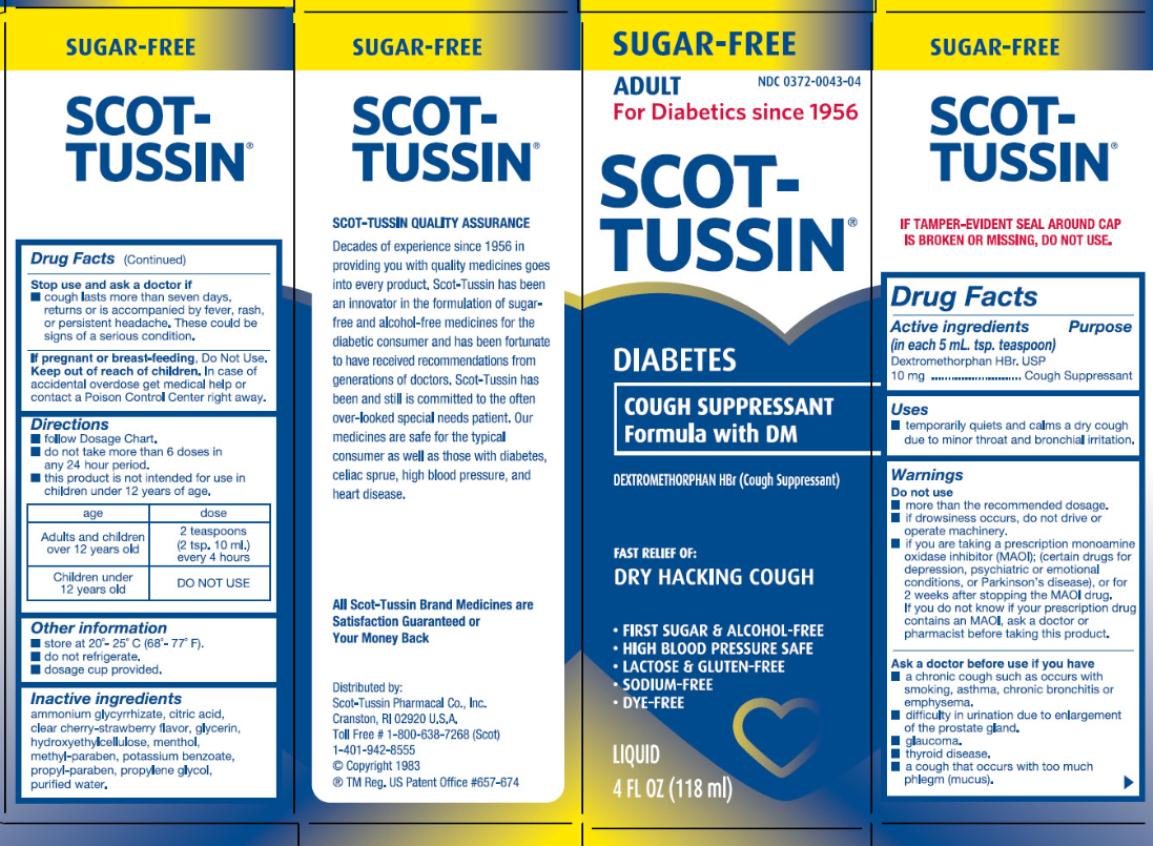 DRUG LABEL: Scot-Tussin Diabetes Cough Formula with DM
NDC: 0372-0043 | Form: LIQUID
Manufacturer: SCOT-TUSSIN Pharmacal Co., Inc.
Category: otc | Type: HUMAN OTC DRUG LABEL
Date: 20130121

ACTIVE INGREDIENTS: DEXTROMETHORPHAN HYDROBROMIDE 10 mg/5 mL
INACTIVE INGREDIENTS: AMMONIUM GLYCYRRHIZATE; CITRIC ACID MONOHYDRATE; GLYCERIN; HYDROXYETHYL CELLULOSE (2000 MPA.S AT 1%); MENTHOL; METHYLPARABEN; POTASSIUM BENZOATE; PROPYLENE GLYCOL; PROPYLPARABEN; WATER

Scot-Tussin Diabetes Cough Formula with DM

Active Ingredient

(in each 5 mL. tsp. teaspoon)

Dextromethorphan HBr. USP 10mg

Purpose

Cough Suppressant

Uses

- Temporarily quiets and calms a dry cough due to minor throat and bronchial irritation.

Warnings

Do not use

- more than the recommended dosage.
- If drowsiness occurs, do not drive or operate machinery.
- if you are now taking a prescription monoamine oxidase inhibitor (MAOI) (certain drugs for depression, psychiatric, or emotional conditions, or Parkinson’s disease) or for two weeks after stopping the MAOI drug. If you do not know if your prescription drug contains an MAOI, ask a doctor or pharmacists before taking this product.

Ask a doctor before use is you have

- a chronic cough such as occurs with smoking, asthma, chronic bronchitis or emphysema.
- difficulty in urination due to enlargement of the prostate gland.
- Glaucoma.
- Thyroid disease.
- a chough that occurs with too much phlegm (mucus).

Stop use and ask a doctor if

- Cough lasts more than seven days, returns or is accompanied by fever, rash or persistent headache. These could be signs of a serious condition.

If pregnant or breast-feeding,

Do Not Use.

Keep out of reach of children.

In case of accidental overdose get medical help or contact a poison control center right away.

Directions

- Follow Dosage Chart.
- Do not take more than 6 doses in any 24 hour period.
- This product is not intended for use in children under 12 years of age.

age | dose
Adults and children over 12 years old | 2 teaspoons (2 tsp. 10 ml) every 4 hours
Children Under 12 years old | DO NOT USE

Other Information

- Store at 20º – 25º C (68º – 77º F).
- Do not refrigerate.
- Dosage cup provided.

Inactive Ingredients

Ammonium Glycyrrhizate, Citric Acid, Clear Cherry-Strawberry Flavor, Glycerin, Hydroxyethylcellulose, Menthol, Methyl Paraben, Potassium Benzoate, Propyl Paraben, Propylene Glycol, Purified Water.

Principal Display Panel

NDC 0372-0043-04
SCOT-TUSSIN
DIABETES
COUGH SUPPRESASANT Formula with DM

4 FL OZ (118 ml)